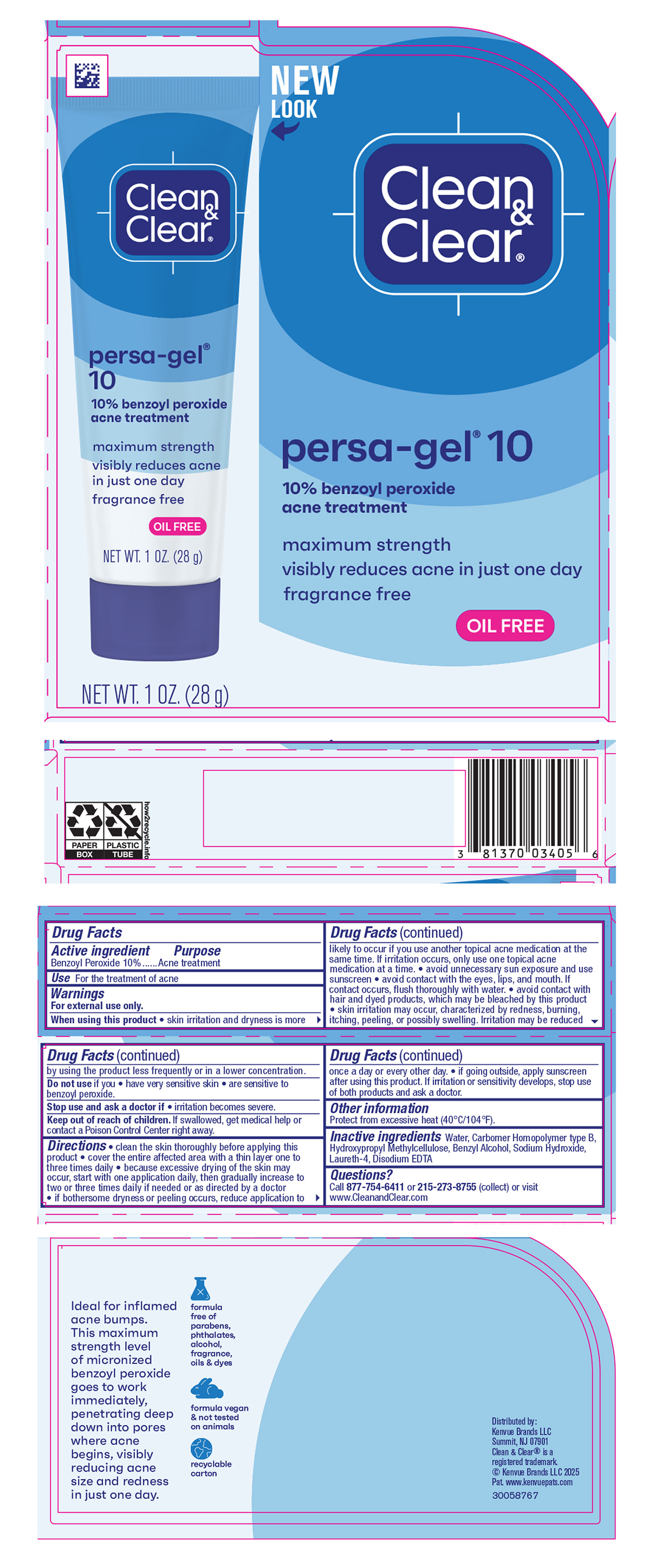 DRUG LABEL: Clean and Clear persa-gel 10 Maximum Strength
NDC: 69968-0720 | Form: GEL
Manufacturer: Kenvue Brands LLC
Category: otc | Type: HUMAN OTC DRUG LABEL
Date: 20250512

ACTIVE INGREDIENTS: BENZOYL PEROXIDE 100 mg/1 g
INACTIVE INGREDIENTS: BENZYL ALCOHOL; WATER; CARBOMER HOMOPOLYMER TYPE B (ALLYL PENTAERYTHRITOL CROSSLINKED); HYPROMELLOSE, UNSPECIFIED; SODIUM HYDROXIDE; LAURETH-4; EDETATE DISODIUM ANHYDROUS

Clean and Clear Persa Gel 10 Maximum Strength

Drug Facts

Active ingredient

Benzoyl Peroxide 10%

Purpose

Acne treatment

Use

For the treatment of acne.

Warnings

For external use only.

When using this product

- skin irritation and dryness is more likely to occur if you use another topical acne medication at the same time. If irritation occurs, only use one topical acne medication at a time.
- avoid unnecessary sun exposure and use sunscreen
- avoid contact with the eyes, lips, and mouth. If contact occurs, flush thoroughly with water.
- avoid contact with hair and dyed products, which may be bleached by this product
- skin irritation may occur, characterized by redness, burning, itching, peeling, or possibly swelling. Irritation may be reduced by using the product less frequently or in a lower concentration .

Do not use if you

- have very sensitive skin
- are sensitive to benzoyl peroxide.

Stop use and ask a doctor if

- irritation becomes severe .

Keep out of reach of children. If swallowed, get medical help or contact a Poison Control Center right away.

Directions

- clean the skin thoroughly before applying this product
- cover the entire affected area with a thin layer one to three times daily
- because excessive drying of the skin may occur, start with one application daily, then gradually increase to two or three times daily if needed or as directed by a doctor
- if bothersome dryness or peeling occurs, reduce application to once a day or every other day.
- if going outside, apply sunscreen after using this product. If irritation or sensitivity develops, stop use of both products and ask a doctor.

Other information

Protect from excessive heat (40°C/104°F).

Inactive ingredients

Water, Carbomer Homopolymer type B, Hydroxypropyl Methylcellulose, Benzyl Alcohol, Sodium Hydroxide, Laureth-4, Disodium EDTA

Questions?

Call 877-754-6411 or 215-273-8755 (collect) or visit www.CleanandClear.com

Distributed by:
Kenvue Brands LLC
Summit, NJ 07901

PRINCIPAL DISPLAY PANEL

NEW

LOOK

Clean

&

Clear®

persa-gel® 10

10% benzoyl peroxide

acne treatment

maximum strength

visibly reduces acne in just one day

fragrance free

OIL FREE

NET WT. 1 OZ. (28g)